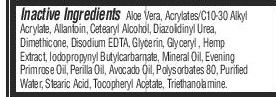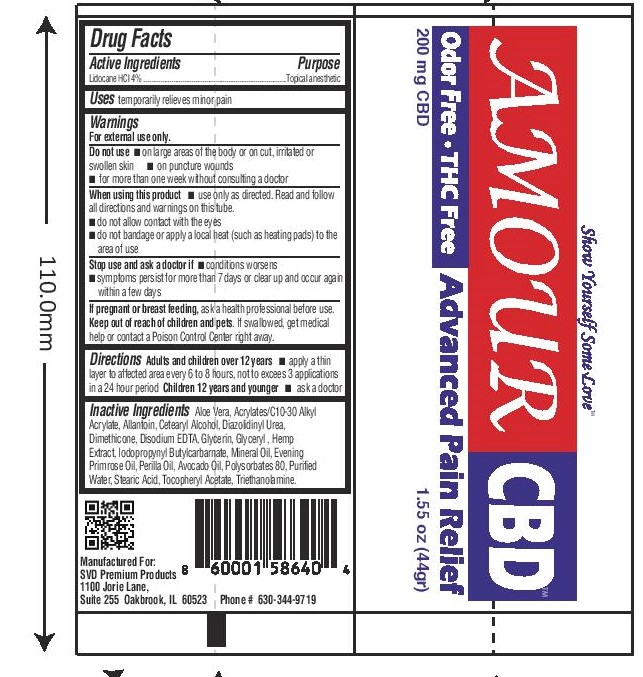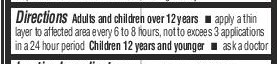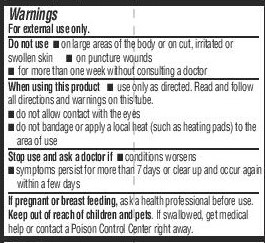 DRUG LABEL: Amour CBD
NDC: 72897-001 | Form: CREAM
Manufacturer: SVD Premium Products
Category: otc | Type: HUMAN OTC DRUG LABEL
Date: 20260107

ACTIVE INGREDIENTS: LIDOCAINE HYDROCHLORIDE 4 mg/100 g
INACTIVE INGREDIENTS: DIAZOLIDINYL UREA; ALLANTOIN; AVOCADO OIL; CARBOMER INTERPOLYMER TYPE A (55000 CPS); ALOE VERA LEAF; CETYL ALCOHOL; POLYSORBATE 80; STEARIC ACID; TROLAMINE; PERILLA FRUTESCENS SEED OIL; DIMETHICONE; EDETATE DISODIUM ANHYDROUS; EVENING PRIMROSE OIL; WATER; .ALPHA.-TOCOPHEROL ACETATE; IODOPROPYNYL BUTYLCARBAMATE; GLYCERIN; GLYCERYL MONOSTEARATE; CANNABIDIOL; MINERAL OIL

Amour CBD 4% Lidocaine

ACTIVE INGREDIENT

Lidocaine HCl 4%

Keep out of reach of children and pets. If swallowed, get medical help or contact a Poison Control Center right away

PURPOSE

Topical analgesic

INDICATIONS AND USAGE

Temporarily relieves minor pain